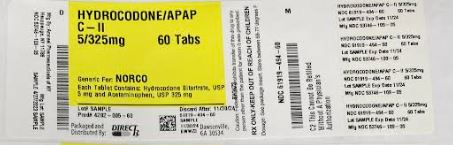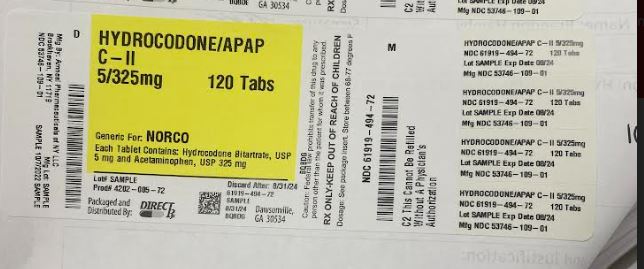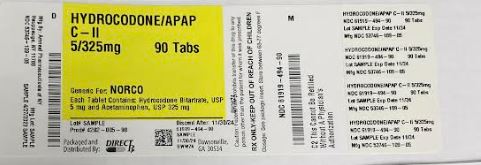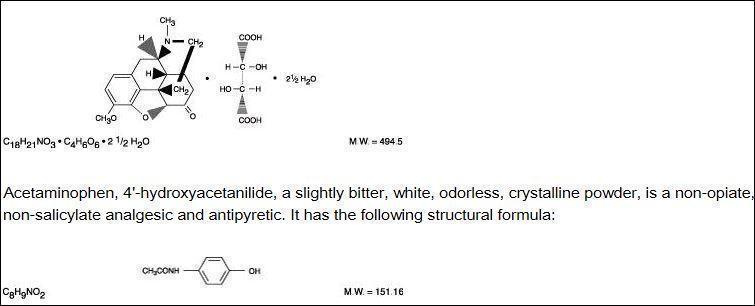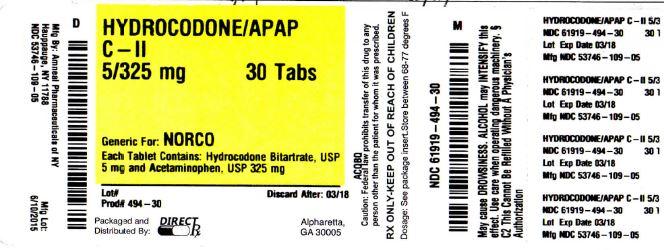 DRUG LABEL: HYDROCODONE BITARTRATE
NDC: 61919-494 | Form: TABLET
Manufacturer: DIRECT RX
Category: prescription | Type: HUMAN PRESCRIPTION DRUG LABEL
Date: 20230427
DEA Schedule: CII

ACTIVE INGREDIENTS: HYDROCODONE BITARTRATE 5 mg/1 1; ACETAMINOPHEN 325 mg/1 1
INACTIVE INGREDIENTS: CROSPOVIDONE; POVIDONE; STARCH, CORN; STEARIC ACID

HYDROCODONE BITARTRATE

BOXED WARNING SECTION

Acetaminophen has been associated with cases of acute liver failure, at times resulting in liver transplant and death. Most of the cases of liver injury are associated with the use of acetaminophen at doses that exceed 4000 milligrams per day, and often involve more than one acetaminophen-containing product.

DESCRIPTION SECTION

Hydrocodone Bitartrate and Acetaminophen Tablets, USP are supplied in tablet form for oral administration.

Hydrocodone bitartrate is an opioid analgesic and antitussive and occurs as fine, white crystals or as a crystalline powder. It is affected by light. The chemical name is: 4,5α-epoxy-3-methoxy-17-methylmorphinan-6-one tartrate (1:1) hydrate (2:5). It has the following structural formula:

Each Hydrocodone Bitartrate and Acetaminophen Tablet, USP contains:

Hydrocodone Bitartrate, USP ........................... 5 mg

Acetaminophen, USP .................................... 325 mg

In addition, each tablet contains the following inactive ingredients: colloidal silicon dioxide, crospovidone, magnesium stearate, microcrystalline cellulose, povidone, pregelatinized starch and stearic acid.

Meets USP Dissolution Test 1.

CLINICAL PHARMACOLOGY SECTION

Hydrocodone is a semisynthetic narcotic analgesic and antitussive with multiple actions qualitatively similar to those of codeine. Most of these involve the central nervous system and smooth muscle. The precise mechanism of action of hydrocodone and other opiates is not known, although it is believed to relate to the existence of opiate receptors in the central nervous system. In addition to analgesia, narcotics may produce drowsiness, changes in mood and mental clouding.

The analgesic action of acetaminophen involves peripheral influences, but the specific mechanism is as yet undetermined. Antipyretic activity is mediated through hypothalamic heat regulating centers. Acetaminophen inhibits prostaglandin synthetase. Therapeutic doses of acetaminophen have negligible effects on the cardiovascular or respiratory systems; however, toxic doses may cause circulatory failure and rapid, shallow breathing.

Pharmacokinetics

The behavior of the individual components is described below.

Hydrocodone: Following a 10 mg oral dose of hydrocodone administered to five adult male subjects, the mean peak concentration was 23.6 ± 5.2 ng/mL. Maximum serum levels were achieved at 1.3 ± 0.3 hours and the half-life was determined to be 3.8 ± 0.3 hours. Hydrocodone exhibits a complex pattern of metabolism including O-demethylation, N-demethylation and 6-keto reduction to the corresponding 6-α- and 6-β-hydroxymetabolites. See OVERDOSAGE for toxicity information.

Acetaminophen: Acetaminophen is rapidly absorbed from the gastrointestinal tract and is distributed throughout most body tissues. The plasma half-life is 1.25 to 3 hours, but may be increased by liver damage and following overdosage. Elimination of acetaminophen is principally by liver metabolism (conjugation) and subsequent renal excretion of metabolites. Approximately 85% of an oral dose appears in the urine within 24 hours of administration, most as the glucuronide conjugate, with small amounts of other conjugates and unchanged drug. See OVERDOSAGE for toxicity information

INDICATIONS & USAGE SECTION

Hydrocodone bitartrate and acetaminophen tablets, USP are indicated for the relief of moderate to moderately severe pain.

CONTRAINDICATIONS SECTION

This product should not be administered to patients who have previously exhibited hypersensitivity to hydrocodone or acetaminophen, or any other component of this product.

Patients known to be hypersensitive to other opioids may exhibit cross sensitivity to hydrocodone.

WARNINGS SECTION

Hepatotoxicity

Acetaminophen has been associated with cases of acute liver failure, at times resulting in liver transplant and death. Most of the cases of liver injury are associated with the use of acetaminophen at doses that exceed 4000 milligrams per day, and often involve more than one acetaminophen-containing product. The excessive intake of acetaminophen may be intentional to cause self-harm or unintentional as patients attempt to obtain more pain relief or unknowingly take other acetaminophen-containing products.

The risk of acute liver failure is higher in individuals with underlying liver disease and in individuals who ingest alcohol while taking acetaminophen.

Instruct patients to look for acetaminophen or APAP on package labels and not to use more than one product that contains acetaminophen. Instruct patients to seek medical attention immediately upon ingestion of more than 4000 milligrams of acetaminophen per day, even if they feel well.

Serious skin reactions

Rarely, acetaminophen may cause serious skin reactions such as acute generalized exanthematous pustulosis (AGEP), Stevens-Johnson Syndrome (SJS), and toxic epidermal necrolysis (TEN), which can be fatal. Patients should be informed about the signs of serious skin reactions, and use of the drug should be discontinued at the first appearance of skin rash or any other sign of hypersensitivity.

Hypersensitivity/ anaphylaxis

There have been post-marketing reports of hypersensitivity and anaphylaxis associated with use of acetaminophen. Clinical signs include swelling of the face, mouth, and throat, respiratory distress, urticaria, rash, pruritis, and vomiting. There were infrequent reports of life-threatening anaphylaxis requiring emergency medical attention. Instruct patients to discontinue Hydrocodone Bitartrate and Acetaminophen Tablets, USP immediately and seek medical care if they experience these symptoms. Do not prescribe Hydrocodone Bitartrate and Acetaminophen Tablets, USP for patients with acetaminophen allergy.

Respiratory Depression

At high doses or in sensitive patients, hydrocodone may produce dose-related respiratory depression by acting directly on the brain stem respiratory center. Hydrocodone also affects the center that controls respiratory rhythm, and may produce irregular and periodic breathing.

Head Injury and Increased Intracranial Pressure

The respiratory depressant effects of narcotics and their capacity to elevate cerebrospinal fluid pressure may be markedly exaggerated in the presence of head injury, other intracranial lesions or a preexisting increase in intracranial pressure. Furthermore, narcotics produce adverse reactions which may obscure the clinical course of patients with head injuries.

Acute Abdominal Conditions

The administration of narcotics may obscure the diagnosis or clinical course of patients with acute abdominal conditions.

Misuse, Abuse, and Diversion of Opioids

Hydrocodone bitartrate and acetaminophen tablets contain hydrocodone, an opioid agonist, and is a Schedule III controlled substance. Opioid agonists have the potential for being abused and are sought by abusers and people with addiction disorders, and are subject to diversion.

Hydrocodone bitartrate and acetaminophen tablets can be abused in a manner similar to other opioid agonists, legal or illicit. This should be considered when prescribing or dispensing Hydrocodone bitartrate and acetaminophen tablets in situations where the physician or pharmacist is concerned about an increased risk of misuse, abuse or diversion (see DRUG ABUSE AND DEPENDENCE).

PRECAUTIONS SECTION

General

Special Risk Patients: As with any narcotic analgesic agent, hydrocodone bitartrate and acetaminophen tablets should be used with caution in elderly or debilitated patients and those with severe impairment of hepatic or renal function, hypothyroidism, Addison's disease, prostatic hypertrophy or urethral stricture. The usual precautions should be observed and the possibility of respiratory depression should be kept in mind.

Cough Reflex: Hydrocodone suppresses the cough reflex; as with all narcotics, caution should be exercised when hydrocodone bitartrate and acetaminophen tablets are used postoperatively and in patients with pulmonary disease.

Information for Patients/Careivers

- •Do not take Hydrocodone Bitartrate and Acetaminophen Tablets, USP if you are allergic to any of its ingredients.
- •If you develop signs of allergy such as a rash or difficulty breathing, stop taking Hydrocodone Bitartrate and Acetaminophen Tablets, USP and contact your healthcare provider immediately.
- •Do not take more than 4000 milligrams of acetaminophen per day. Call your doctor if you took more than the recommended dose.

Hydrocodone, like all narcotics, may impair the mental and/or physical abilities required for the performance of potentially hazardous tasks such as driving a car or operating machinery; patients should be cautioned accordingly.

Alcohol and other CNS depressants may produce an additive CNS depression, when taken with this combination product, and should be avoided.

Hydrocodone may be habit-forming. Patients should take the drug only for as long as it is prescribed, in the amounts prescribed, and no more frequently than prescribed.

Laboratory Tests

In patients with severe hepatic or renal disease, effects of therapy should be monitored with serial liver and/or renal function tests.

Drug Interactions

Patients receiving other narcotic analgesics, antihistamines, antipsychotics, anti-anxiety agents, or other CNS depressants (including alcohol) concomitantly with hydrocodone bitartrate and acetaminophen tablets may exhibit an additive CNS depression. When combined therapy is contemplated, the dose of one or both agents should be reduced.

The use of MAO inhibitors or tricyclic antidepressants with hydrocodone preparations may increase the effect of either the antidepressant or hydrocodone.

Drug/Laboratory Test Interactions

Acetaminophen may produce false-positive test results for urinary 5-hydroxyindoleacetic acid.

Carcinogenesis, Mutagenesis, Impairment of Fertility

No adequate studies have been conducted in animals to determine whether hydrocodone or acetaminophen have a potential for carcinogenesis, mutagenesis, or impairment of fertility.

Pregnancy

Teratogenic Effects: Pregnancy Category C: There are no adequate and well-controlled studies in pregnant women. Hydrocodone bitartrate and acetaminophen tablets should be used during pregnancy only if the potential benefit justifies the potential risk to the fetus.

Nonteratogenic Effects: Babies born to mothers who have been taking opioids regularly prior to delivery will be physically dependent. The withdrawal signs include irritability and excessive crying, tremors, hyperactive reflexes, increased respiratory rate, increased stools, sneezing, yawning, vomiting, and fever. The intensity of the syndrome does not always correlate with the duration of maternal opioid use or dose. There is no consensus on the best method of managing withdrawal.

Labor and Delivery

As with all narcotics, administration of this product to the mother shortly before delivery may result in some degree of respiratory depression in the newborn, especially if higher doses are used.

Nursing Mothers

Acetaminophen is excreted in breast milk in small amounts, but the significance of its effects on nursing infants is not known. It is not known whether hydrocodone is excreted in human milk. Because many drugs are excreted in human milk and because of the potential for serious adverse reactions in nursing infants from hydrocodone and acetaminophen, a decision should be made whether to discontinue nursing or to discontinue the drug, taking into account the importance of the drug to the mother.

Pediatric Use

Safety and effectiveness in pediatric patients have not been established.

Geriatric Use

Clinical studies of hydrocodone bitartrate and acetaminophen did not include sufficient numbers of subjects aged 65 and over to determine whether they respond differently from younger subjects. Other reported clinical experience has not identified differences in responses between the elderly and younger patients. In general, dose selection for an elderly patient should be cautious, usually starting at the low end of the dosing range, reflecting the greater frequency of decreased hepatic, renal, or cardiac function, and of concomitant disease or other drug therapy.

Hydrocodone and the major metabolites of acetaminophen are known to be substantially excreted by the kidney. Thus the risk of toxic reactions may be greater in patients with impaired renal function due to the accumulation of the parent compound and/or metabolites in the plasma. Because elderly patients are more likely to have decreased renal function, care should be taken in dose selection, and it may be useful to monitor renal function.

Hydrocodone may cause confusion and over-sedation in the elderly; elderly patients generally should be started on low doses of hydrocodone bitartrate and acetaminophen tablets and observed closely.

ADVERSE REACTIONS SECTION

The most frequently reported adverse reactions are light-headedness, dizziness, sedation, nausea and vomiting. These effects seem to be more prominent in ambulatory than in non-ambulatory patients, and some of these adverse reactions may be alleviated if the patient lies down.

Other adverse reactions include:

Central Nervous System: Drowsiness, mental clouding, lethargy, impairment of mental and physical performance, anxiety, fear, dysphoria, psychic dependence, mood changes.

Gastrointestinal System: Prolonged administration of hydrocodone bitartrate and acetaminophen tablets may produce constipation.

Genitourinary System: Ureteral spasm, spasm of vesical sphincters and urinary retention have been reported with opiates.

Respiratory Depression: Hydrocodone bitartrate may produce dose-related respiratory depression by acting directly on the brain stem respiratory centers (see OVERDOSAGE).

Special Senses: Cases of hearing impairment or permanent loss have been reported predominantly in patients with chronic overdose.

Dermatological: Skin rash, pruritus.

The following adverse drug events may be borne in mind as potential effects of acetaminophen: allergic reactions, rash, thrombocytopenia, agranulocytosis. Potential effects of high dosage are listed in the OVERDOSAGE section.

DRUG ABUSE AND DEPENDENCE SECTION

Misuse, Abuse, and Diversion of Opioids

Hydrocodone bitartrate and acetaminophen tablets contain hydrocodone, an opioid agonist, and is a Schedule III controlled substance. Hydrocodone bitartrate and acetaminophen tablets, and other opioids, used in analgesia can be abused and are subject to criminal diversion.

Addiction is a primary, chronic, neurobiologic disease, with genetic, psychosocial, and environmental factors influencing its development and manifestations. It is characterized by behaviors that include one or more of the following: impaired control over drug use, compulsive use, continued use despite harm, and craving. Drug addiction is a treatable disease utilizing a multidisciplinary approach, but relapse is common.

“Drug seeking” behavior is very common in addicts and drug abusers. Drug-seeking tactics include emergency calls or visits near the end of office hours, refusal to undergo appropriate examination, testing or referral, repeated “loss” of prescriptions, tampering with prescriptions and reluctance to provide prior medical records or contact information for other treating physician(s). “Doctor shopping” to obtain additional prescriptions is common among drug abusers and people suffering from untreated addiction.

Abuse and addiction are separate and distinct from physical dependence and tolerance. Physical dependence usually assumes clinically significant dimensions only after several weeks of continued opioid use, although a mild degree of physical dependence may develop after a few days of opioid therapy. Tolerance, in which increasingly large doses are required in order to produce the same degree of analgesia, is manifested initially by a shortened duration of analgesic effect, and subsequently by decreases in the intensity of analgesia. The rate of development of tolerance varies among patients. Physicians should be aware that abuse of opioids can occur in the absence of true addiction and is characterized by misuse for non-medical purposes, often in combination with other psychoactive substances. Hydrocodone bitartrate and acetaminophen tablets, like other opioids, may be diverted for non-medical use. Record-keeping of prescribing information, including quantity, frequency, and renewal requests is strongly advised.

Proper assessment of the patient, proper prescribing practices, periodic re-evaluation of therapy, and proper dispensing and storage are appropriate measures that help to limit abuse of opioid drugs.

OVERDOSAGE SECTION

Following an acute overdosage, toxicity may result from hydrocodone or acetaminophen.

Signs and Symptoms

Hydrocodone: Serious overdose with hydrocodone is characterized by respiratory depression (a decrease in respiratory rate and/or tidal volume, Cheyne-Stokes respiration, cyanosis), extreme somnolence progressing to stupor or coma, skeletal muscle flaccidity, cold and clammy skin, and sometimes bradycardia and hypotension. In severe overdosage, apnea, circulatory collapse, cardiac arrest and death may occur.

Acetaminophen: In acetaminophen overdosage: dose-dependent, potentially fatal hepatic necrosis is the most serious adverse effect. Renal tubular necrosis, hypoglycemic coma and coagulation defects may also occur.

Early symptoms following a potentially hepatotoxic overdose may include: nausea, vomiting, diaphoresis and general malaise. Clinical and laboratory evidence of hepatic toxicity may not be apparent until 48 to 72 hours post-ingestion.

Treatment

A single or multiple drug overdose with hydrocodone and acetaminophen is a potentially lethal polydrug overdose, and consultation with a regional poison control center is recommended.

Immediate treatment includes support of cardiorespiratory function and measures to reduce drug absorption. Oxygen, intravenous fluids, vasopressors, and other supportive measures should be employed as indicated. Assisted or controlled ventilation should also be considered.

For hydrocodone overdose, primary attention should be given to the reestablishment of adequate respiratory exchange through provision of a patent airway and the institution of assisted or controlled ventilation. The narcotic antagonist naloxone hydrochloride is a specific antidote against respiratory depression which may result from overdosage or unusual sensitivity to narcotics, including hydrocodone. Since the duration of action of hydrocodone may exceed that of the antagonist, the patient should be kept under continued surveillance, and repeated doses of the antagonist should be administered as needed to maintain adequate respiration. A narcotic antagonist should not be administered in the absence of clinically significant respiratory or cardiovascular depression.

Gastric decontamination with activated charcoal should be administered just prior to N-acetylcysteine (NAC) to decrease systemic absorption if acetaminophen ingestion is known or suspected to have occurred within a few hours of presentation. Serum acetaminophen levels should be obtained immediately if the patient presents 4 hours or more after ingestion to assess potential risk of hepatotoxicity; acetaminophen levels drawn less than 4 hours post-ingestion may be misleading. To obtain the best possible outcome, NAC should be administered as soon as possible where impending or evolving liver injury is suspected. Intravenous NAC may be administered when circumstances preclude oral administration.

Vigorous supportive therapy is required in severe intoxication. Procedures to limit the continuing absorption of the drug must be readily performed since the hepatic injury is dose dependent and occurs early in the course of intoxication.

DOSAGE & ADMINISTRATION SECTION

Dosage should be adjusted according to the severity of the pain and the response of the patient. However, it should be kept in mind that tolerance to hydrocodone can develop with continued use and that the incidence of untoward effects is dose related.

The usual adult dosage is one or two tablets every four to six hours as needed for pain. The total daily dose should not exceed 8 tablets.

HOW SUPPLIED SECTION

Hydrocodone Bitartrate and Acetaminophen Tablets, USP, contain hydrocodone bitartrate 5 mg and acetaminophen 325 mg.

They are supplied as white to off-white, scored, oblong biconvex tablets, debossed “IP 109” on obverse and bisected on the reverse.

They are available as follows:

Bottles of 100: NDC 53746-109-01

Bottles of 500: NDC 53746-109-05

Bottles of 1000: NDC 53746-109-10

Storage: Store at 20° to 25°C (68° to 77°F); excursions permitted to 15° to 30°C (59° to 86°F) [See USP Controlled Room Temperature].

Dispense in a tight, light-resistant container with a child-resistant closure.

A Schedule CIII Narcotic.

Manufactured by:

Amneal Pharmaceuticals of NY

Hauppauge, NY 11788

Rev. 12-2013